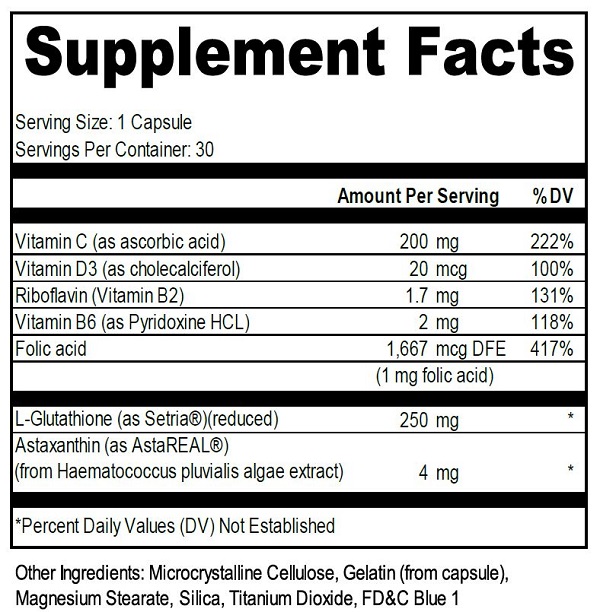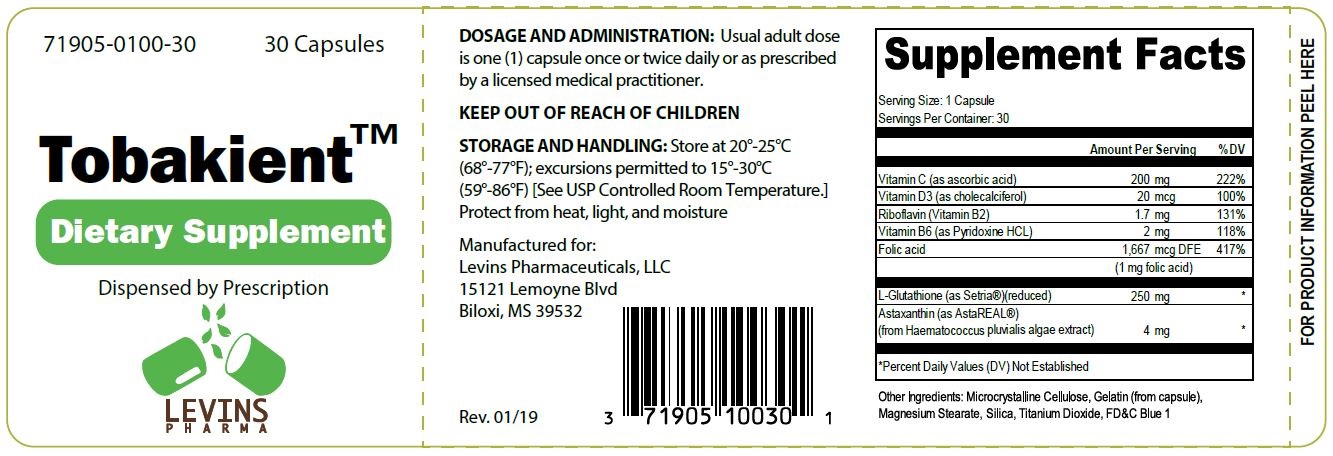 DRUG LABEL: Tobakient
NDC: 71905-100 | Form: CAPSULE
Manufacturer: Levins Pharmaceuticals, LLC
Category: other | Type: Dietary Supplement
Date: 20190220

ACTIVE INGREDIENTS: RIBOFLAVIN 1.7 mg/1 1; ASCORBIC ACID 200 mg/1 1; PYRIDOXINE HYDROCHLORIDE 2 mg/1 1; GLUTATHIONE 250 mg/1 1; CHOLECALCIFEROL 20 ug/1 1; ASTAXANTHIN 4 mg/1 1; FOLIC ACID 1667 ug/1 1
INACTIVE INGREDIENTS: TITANIUM DIOXIDE; FD&C BLUE NO. 1; MAGNESIUM STEARATE; GELATIN; MICROCRYSTALLINE CELLULOSE; SILICON DIOXIDE

Tobakient

STATEMENT OF IDENTITY

Tobakient™ Capsules Dietary Supplement

Health Claim

Dispensed by Prescription†

Tobakient™ is an orally administered prescription vitamin formulation for the clinical dietary management of suboptimal nutritional status in patients experiencing physiologically stressful conditions such as use of tobacco products, or to maintain levels when dietary intake of vitamins is inadequate or excretion or loss is excessive. ††

†This product is a prescription- folic acid with or without other dietary ingredients that – due to increased folic acid levels increased risk associated with masking of B12
deficiency (pernicious anemia) requires administration under the care of a licensed medical practitioner (61 FR 8760). The most appropriate way to ensure pedigree
reporting consistent with these regulatory guidelines and safety monitoring is to dispense this product only by prescription (Rx). This is not an Orange Book product.
This product may be administered only under a physician’s supervision and all prescriptions using this product shall be pursuant to state statutes as applicable. The
ingredients, indication or claims of this product are not to be construed to be drug claims.

1. Federal Register Notice of August 2, 1973 (38 FR 20750)

2. Federal Register Notice of October 17, 1980 (45 FR 69043, 69044)

3. Federal Register Notice of March 5, 1996 (61 FR 8760)

†† These statements have not been evaluated by the Food and Drug Administration. This product is not intended to diagnose, treat, cure or prevent any disease.

WARNINGS

This product is contraindicated in patients with a known hypersensitivity to any of the ingredients.

PRECAUTIONS

Tobakient™ capsules should only be used under the direction and supervision of a licensed medical practitioner. Use with caution in patients that may have a medical condition, are pregnant, lactating, trying to conceive, under the age of 18, or taking medications.

DOSAGE AND ADMINISTRATION

Usual adult dose is one (1) capsule once or twice daily or as prescribed by a licensed medical practitioner.

Tobakient™ capsules are supplied as (blue and white, oblong-shaped) capsules in a child-resistant bottle of 30-count ("71905-0100-30"**).

**Levins Pharmaceuticals does not represent these product codes to be National Drug Codes (NDC). Product codes are formatted according to standard industry practice, to meet the formatting requirement by pedigree reporting and supply-chain control including pharmacies.

SAFE HANDLING WARNING

Store at 20°-25°C (68°-77°F); excursions permitted to 15°-30°C (59°-86°F) [See USP Controlled Room Temperature.]

KEEP OUT OF REACH OF CHILDREN

Tamper evident: Do not use if seal is broken or missing

To report adverse events or to obtain product information, contact 228-392-0043.